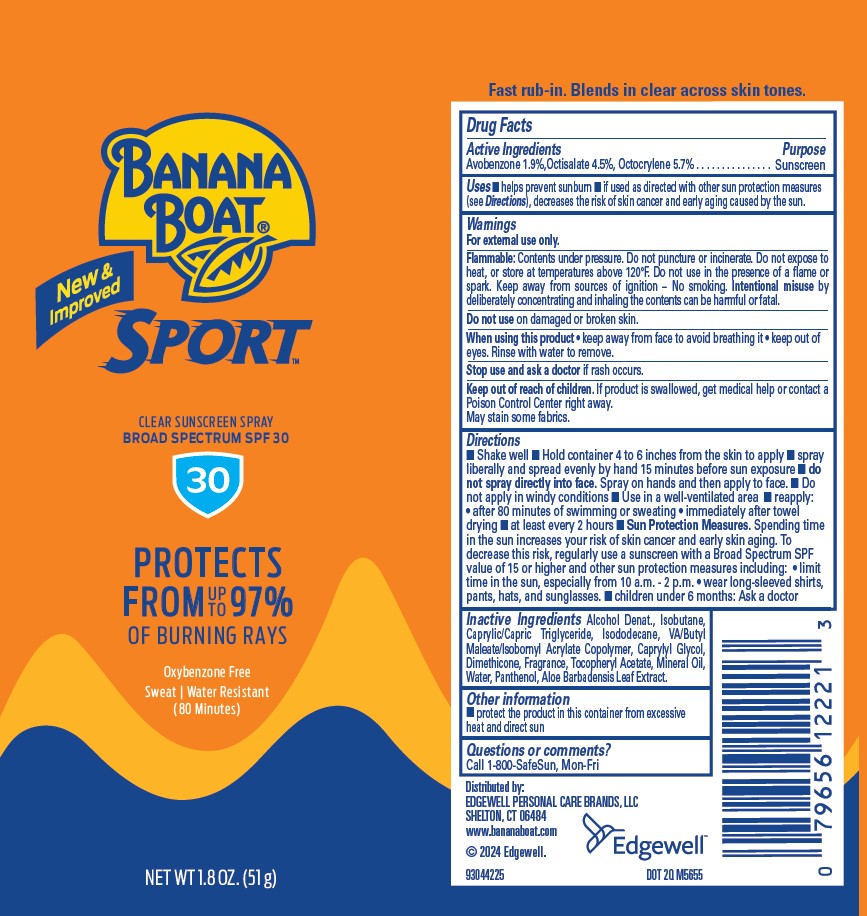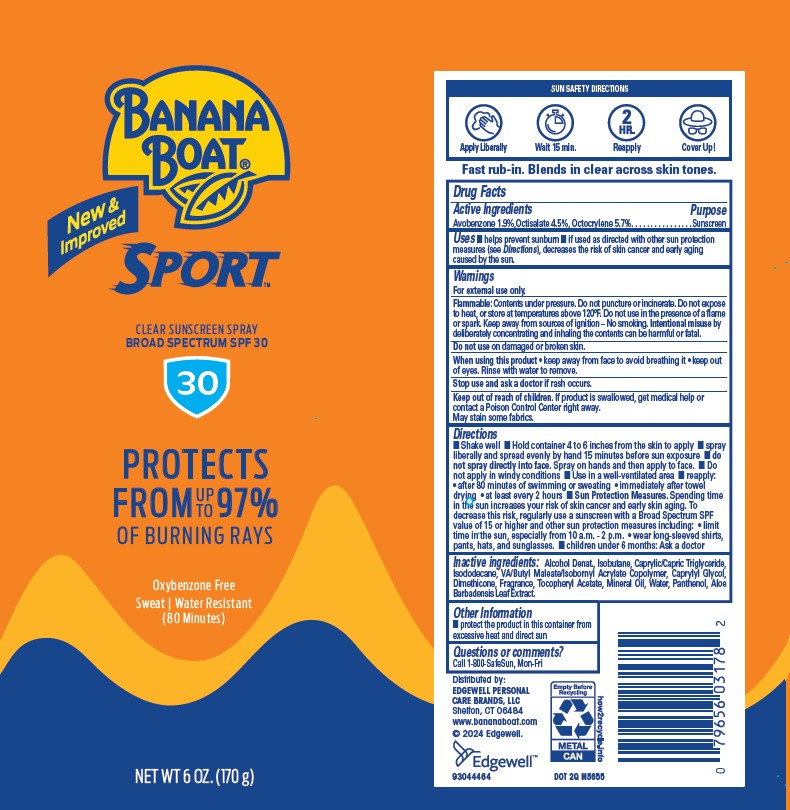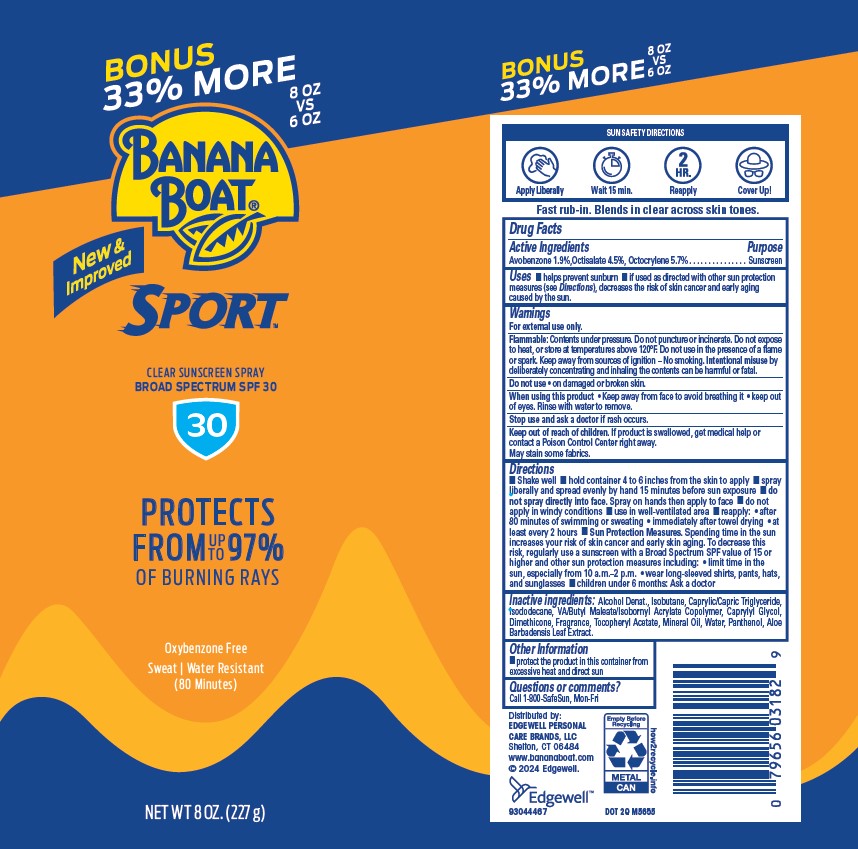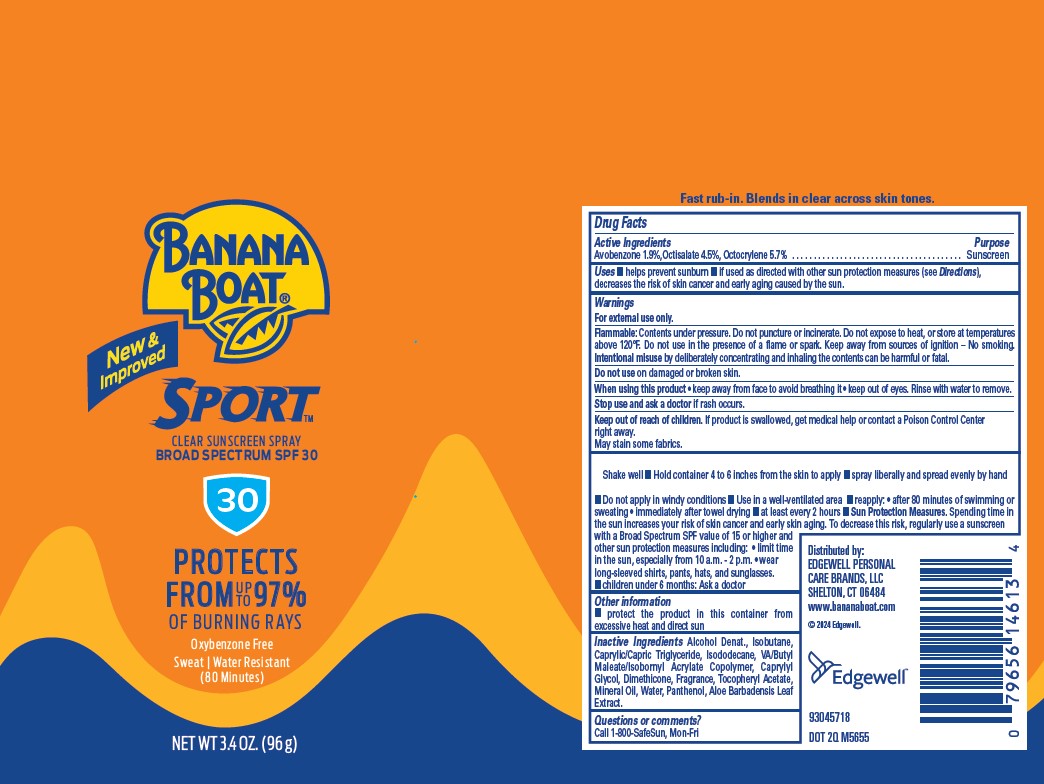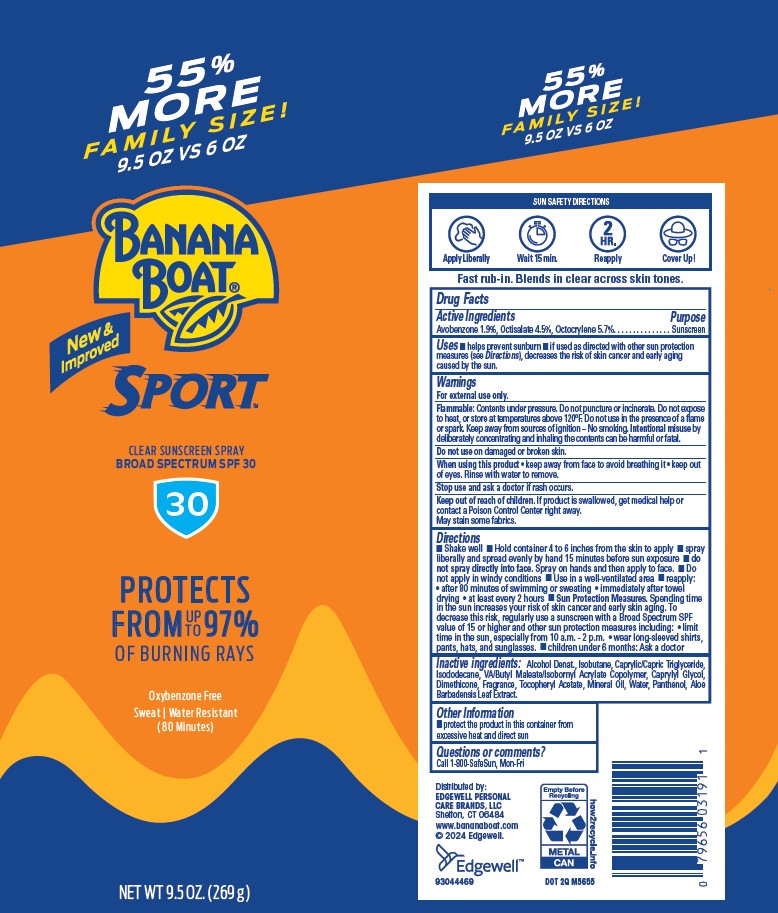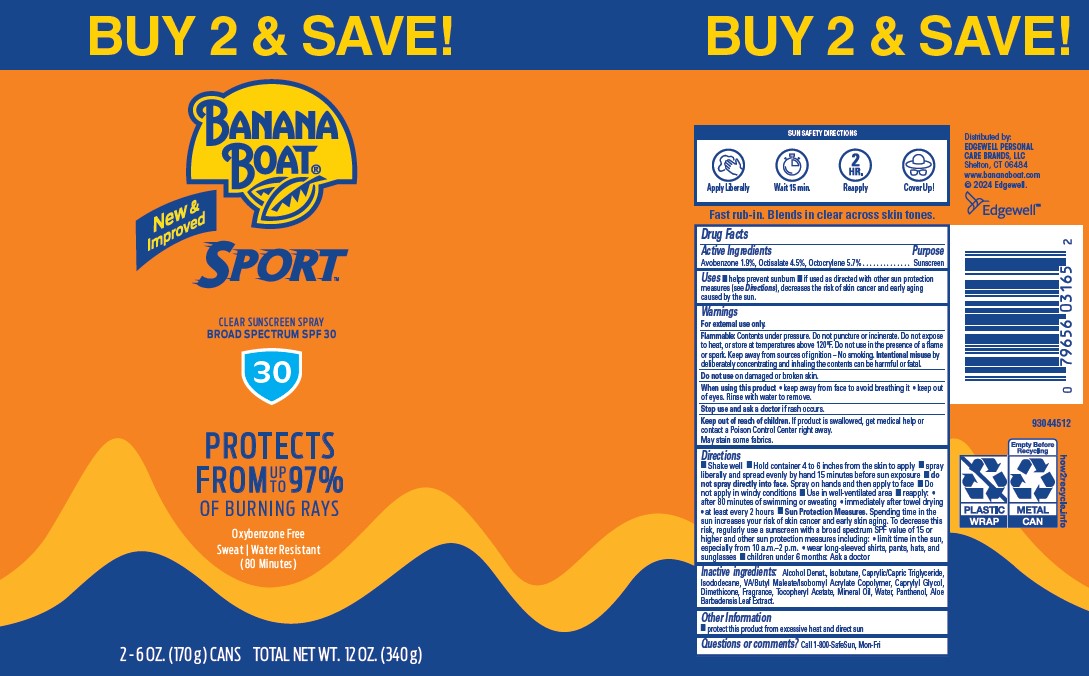 DRUG LABEL: BANANA BOAT
NDC: 63354-433 | Form: AEROSOL, SPRAY
Manufacturer: Edgewell Personal Care Brands LLC
Category: otc | Type: HUMAN OTC DRUG LABEL
Date: 20251117

ACTIVE INGREDIENTS: OCTOCRYLENE 5.7 g/100 g; OCTISALATE 4.5 g/100 g; AVOBENZONE 1.9 g/100 g
INACTIVE INGREDIENTS: MEDIUM-CHAIN TRIGLYCERIDES; CAPRYLYL GLYCOL; ALCOHOL; ISOBUTANE; DIMETHICONE; ALPHA-TOCOPHEROL ACETATE; WATER; PANTHENOL; ALOE VERA LEAF; MINERAL OIL; ISODODECANE

Active Ingredients

Avobenzone 1.9%,Octisalate 4.5%, Octocrylene 5.7% .

Purpose

Sunscreen

Uses

•Uses helps prevent sunburn • if used as directed with other sun protection measures (see Directions), decreases the risk of skin cancer and early aging caused by the sun.

Warnings

For external use only.

Flammable: Contents under pressure. Do not puncture or incinerate. Do not expose to heat, or store at temperatures above 120°F. Do not use in the presence of a flame or spark. Keep away from sources of ignition – No smoking. Intentional misuse by deliberately concentrating and inhaling the contents can be harmful or fatal.

May stain some fabrics.

Do not use

on damaged or broken skin.

When using this product

• Keep away from face to avoid breathing it • keep out of eyes. Rinse with water to remove.

Stop use and ask a doctor

if rash occurs.

Keep out of reach of children.

If product is swallowed, get medical help or contact a Poison Control Center right away.

Directions

• Shake well • hold container 4 to 6 inches from the skin to apply • sprayliberally and spread evenly by hand 15 minutes before sun exposure • do not spray directly into face. Spray on hands then apply to face • do not apply in windy conditions • use in well-ventilated area • reapply: • after 80 minutes of swimming or sweating • immediately after towel drying • at least every 2 hours • Sun Protection Measures. Spending time in the sun increases your risk of skin cancer and early skin aging. To decrease this risk, regularly use a sunscreen with a Broad Spectrum SPF value of 15 or higher and other sun protection measures including: • limit time in the sun, especially from 10 a.m.–2 p.m. • wear long-sleeved shirts, pants, hats, and sunglasses • children under 6 months: Ask a doctor

Inactive ingredients:

Alcohol Denat., Isobutane, Caprylic/Capric Triglyceride,Isododecane, VA/Butyl Maleate/Isobornyl Acrylate Copolymer, Caprylyl Glycol, Dimethicone, Fragrance, Tocopheryl Acetate, Mineral Oil, Water, Panthenol, Aloe Barbadensis Leaf Extract.

Other Information

• protect the product in this container from excessive heat and direct sun

Questions or comments?

Call 1-800-SafeSun, Mon-Fri

PRINCIPAL DISPLAY PANEL

BANANA

BOAT

New &

Improved

SPORT

CLEAR SUNSCREEN SPRAY

BROAD SPECTRUM SPF 30

30

PROTECTS

FROM UP TO 97%

OF BURNING RAYS

Oxybenzone Free

Sweat | Water Resistant

(80 Minutes)

NET WT 1.8 OZ. (51 g)

BANANA

BOAT

New &

Improved

SPORT

CLEAR SUNSCREEN SPRAY

BROAD SPECTRUM SPF 30

30

PROTECTS

FROM UP TO 97%

OF BURNING RAYS

Oxybenzone Free

Sweat | Water Resistant

(80 Minutes)

NET WT 6 OZ. (170 g)

BONUS

33% MORE

8 OZ

VS

6 OZ

BANANA

BOAT

New &

Improved

SPORT

CLEAR SUNSCREEN SPRAY

BROAD SPECTRUM SPF 30

30

PROTECTS

FROM UP TO 97%

OF BURNING RAYS

Oxybenzone Free

Sweat | Water Resistant

(80 Minutes)

NET WT 8 OZ. (227 g)

55%

MORE

FAMILY SIZE!

9.5 OZ VS 6 OZ

BANANA

BOAT

New &

Improved

SPORT

CLEAR SUNSCREEN SPRAY

BROAD SPECTRUM SPF 30

30

PROTECTS

FROM UP TO 97%

OF BURNING RAYS

Oxybenzone Free

Sweat | Water Resistant

(80 Minutes)

NET WT 9.5 OZ. (269 g)

BUY 2 & SAVE!

BANANA

BOAT

New &

Improved

SPORT

CLEAR SUNSCREEN SPRAY

BROAD SPECTRUM SPF 30

30

PROTECTS

FROM UP TO 97%

OF BURNING RAYS

Oxybenzone Free

Sweat | Water Resistant

(80 Minutes)

2 - 6 OZ. (170 g) CANS TOTAL NET WT. 12 OZ. (340 g)

BANANA

BOAT

New &

Improved

SPORT

CLEAR SUNSCREEN SPRAY

BROAD SPECTRUM SPF 30

30

PROTECTS

FROM UP TO 97%

OF BURNING RAYS

Oxybenzone Free

Sweat | Water Resistant

(80 Minutes)

NET WT 3.4 OZ. (96 g)